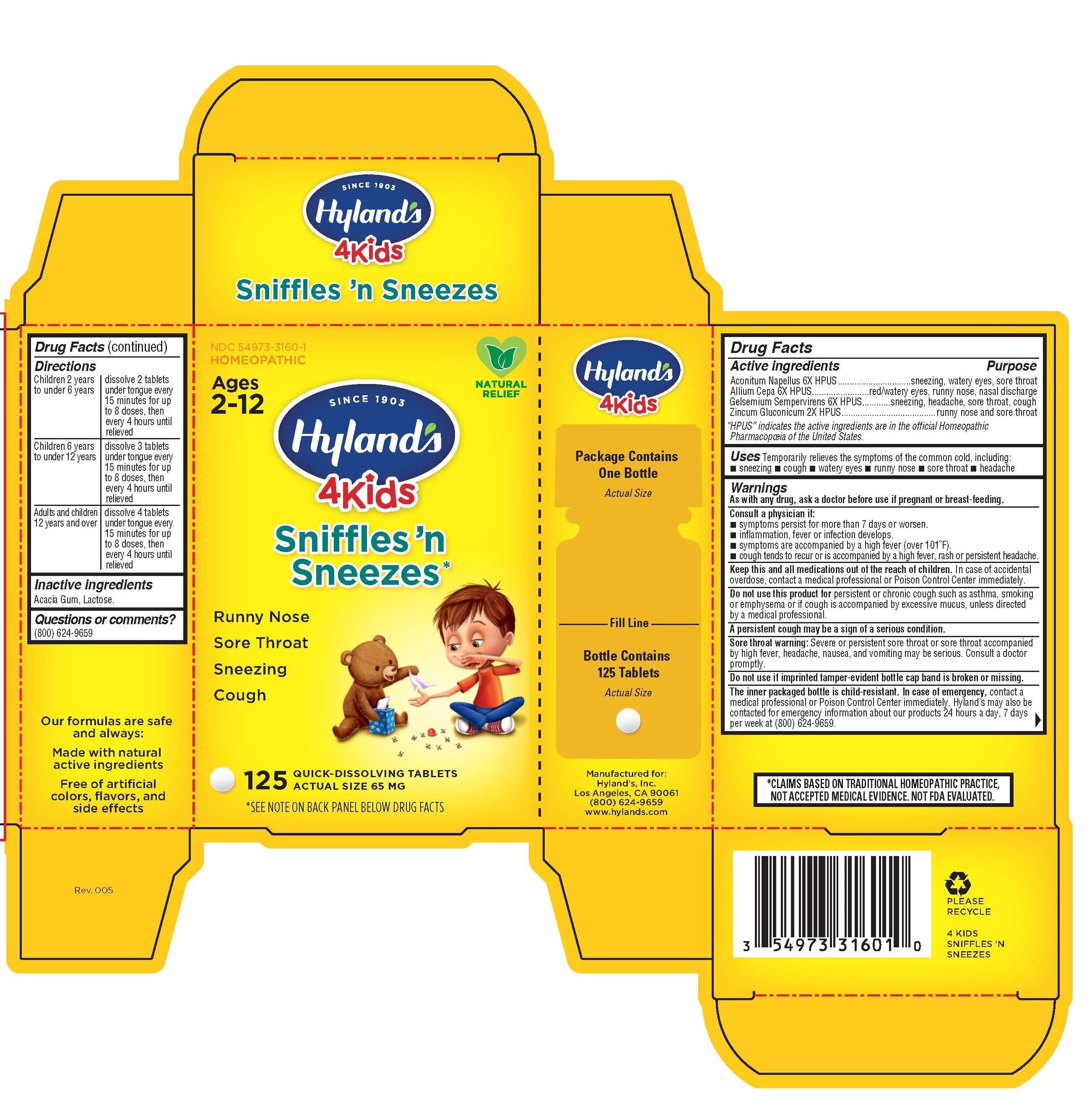 DRUG LABEL: SNIFFLES N SNEEZES 4 KIDS
NDC: 54973-3160 | Form: TABLET
Manufacturer: Hyland's Inc.
Category: homeopathic | Type: HUMAN OTC DRUG LABEL
Date: 20221214

ACTIVE INGREDIENTS: ACONITUM NAPELLUS ROOT 6 [hp_X]/1 1; ONION 6 [hp_X]/1 1; GELSEMIUM SEMPERVIRENS ROOT 6 [hp_X]/1 1; ZINC GLUCONATE 2 [hp_X]/1 1
INACTIVE INGREDIENTS: ACACIA; LACTOSE

Hyland's 4 Kids Sniffles'n Sneezes

Drug Facts

Active ingredients

Active ingredients | Purpose
Acontitum Napellus 6X HPUS | sneezing, watery eyes, sore throat
Allium Cepa 6X HPUS | red/watery eyes, runny nose, nasal discharge
Gelsemium Sempervirens 6X HPUS | sneezing, headache, sore throat, cough
Zincum Gluconium 2X HPUS | runny nose and sore throat

"HPUS" indicates the active ingredients are in the official Homeopathic Pharmacopœia of the United States.

Uses

Uses

Temporarily relieves the symptoms of the common cold, including:

- sneezing
- cough
- watery eyes
- runny nose
- sore throat
- headache

Warnings

As with any drug, ask a doctor before use if pregnant or breast-feeding.

Consult a physician if:

- symptoms persist for more than 7 days or worsen.
- inflammation, fever or infection develops.
- symptoms are accompanied by a high fever (over 101°F).
- cough tends to recur or is accompanied by a high fever, rash or persistent headache.

KEEP OUT OF REACH OF CHILDREN

Keep this and all medications out of the reach of children.

In case of accidental overdose, contact a medical professional or a poison control center immediately.

Do not use this product for persistent or chronic cough such as asthma, smoking or emphysema or if cough is accompanied by excessive mucus, unless directed by a licensed health care professional.

WHEN USING

A persistent cough may be a sign of a serious condition.

Sore throat warning severe or persistent sore throat or sore throat accompanied by high fever, headache, nausea, and vomiting may be serious. Consult a doctor promptly.

Do not use if imprinted tamper-evident bottle cap band is broken or missing.

The inner packaged bottle is child-resistant. In case of emergency, contact a medical professional or Poison Control Center immediately. Hyland’s may also be contacted for emergency information about our products 24 hours a day, 7 days per week at (800) 624-9659.

Drug Facts (continued)

Directions

Children 2 years to under 6 years | dissolve 2 tablets under tongue every 15 minutes for up to 8 doses until relieved; then every 4 hours as required
Children 6 years to under 12 years | dissolve 3 tablets under tongue every 15 minutes for up to 8 doses until relieved; then every 4 hours as required
Adults and children 12 years and over | dissolve 4 tablets under tongue every 15 minutes for up to 8 doses until relieved; then every 4 hours as required

Inactive ingredients

Acacia Gum, Lactose.

Questions or comments?

(800) 624-9659

PRINCIPAL DISPLAY PANEL - 125 Tablet Bottle Carton

Natural
Relief

NDC 54973-3160-1
HOMEOPATHIC

Ages
2-12

SINCE 1903
Hyland's®
4Kids

Sniffles 'n
Sneezes

Runny Nose & Sore Throat

Sneezing

Cough

ACTUAL SIZE 65 MG

125 QUICK-DISSOLVING TABLETS

*SEE NOTE ON BACK PANEL BELOW DRUG FACTS